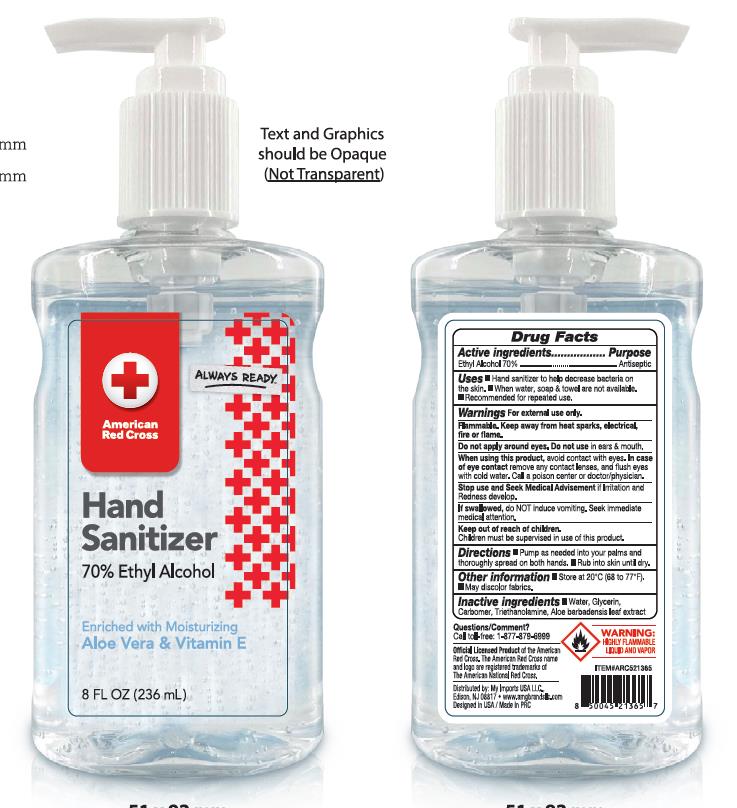 DRUG LABEL: American Red Cross 70% Ethyl Alcohol Hand Sanitizer
NDC: 75742-018 | Form: GEL
Manufacturer: Zhejiang Guoyao Jingyue Aerosol Co., Ltd
Category: otc | Type: HUMAN OTC DRUG LABEL
Date: 20260105

ACTIVE INGREDIENTS: ALCOHOL 70 mL/100 mL
INACTIVE INGREDIENTS: WATER; CARBOMER HOMOPOLYMER, UNSPECIFIED TYPE; GLYCERIN; TROLAMINE; ALOE VERA LEAF

Active ingredients

Ethyl Alcohol 70%

Purpose

Antiseptic

Warnings

For external use only.

Flammable. Keep away from heat sparks, electrical, fire or flame.

DO NOT USE

Do not apply around eyes.Do not use in ears & mouth.

When using this product, avoid contact with eyes. In case of eye contact remove any contact lenses, and flush eyes with cold water. call a poison center or doctor/ physician.

Keep out of reach of children. Children must be supervised in use of this product.

Stop use use and Seek Medical sdvisement if irritation and Redness develop.

ASK DOCTOR

If swallowed, do not induce vomiting. Seek immediate medical attention.

Uses

Hand sanitizer to help decrease bacteria on the skin.

When water, soap & towel are not available.

Recommended for repeated use.

Directions

- Pump as needed into your palms and thoroughly spread on both hands.
- Rub into skin until dry.

Inactive Ingredients

Water

Glycerin

Carbomer

Triethanolamine

Aloe barbadensis leaf extract

Hand Sanitizer 70% Ethyl Alcohol

Enriched with Moisturizing

Aloe Vera & Vitamin E

8 FL OZ(236ml)

Other information

- Store at 20ºC（68-77ºF）
- May discolor fabrics
- Questions/ Comment? Call toll-free:1-877-879-6999